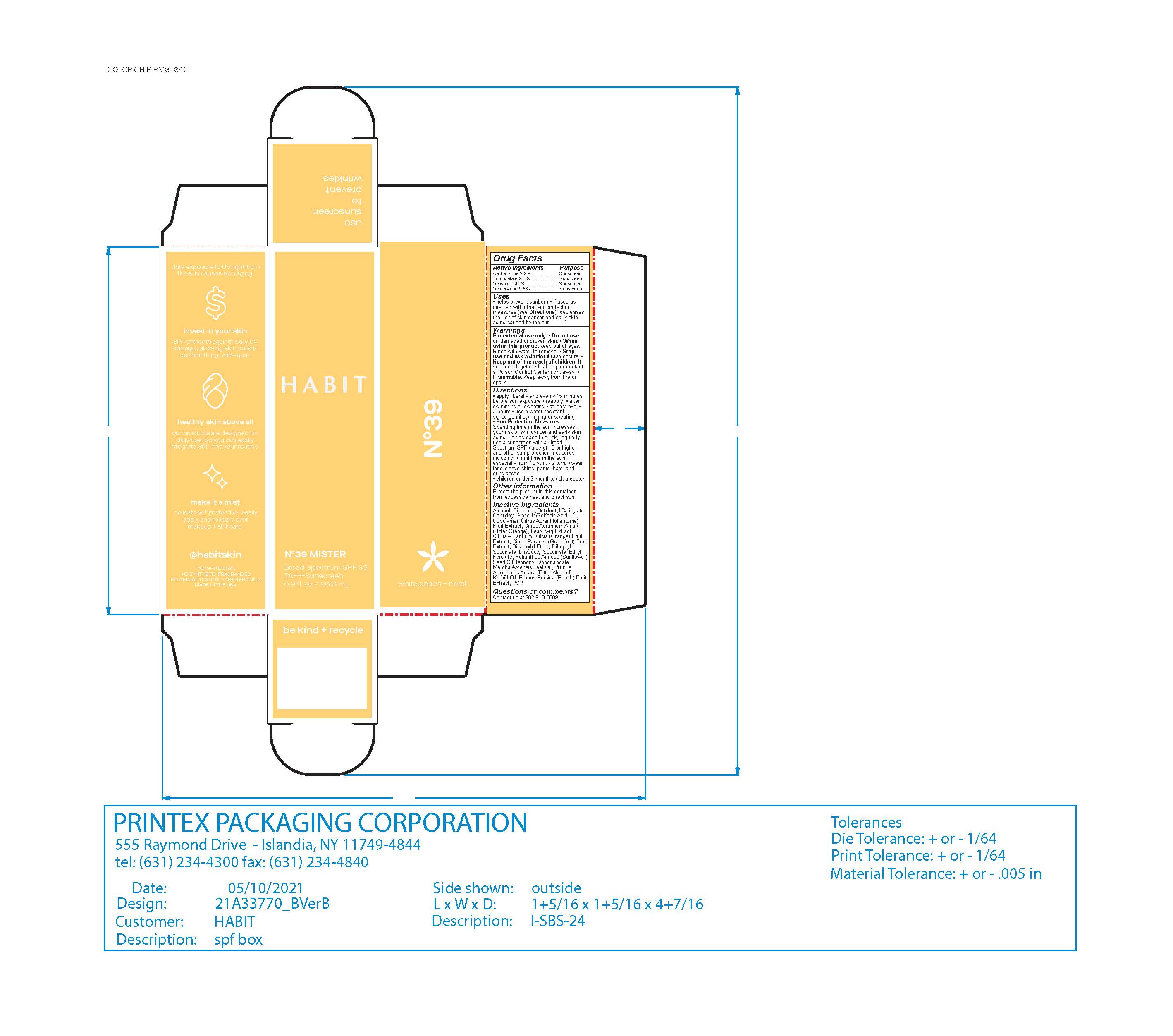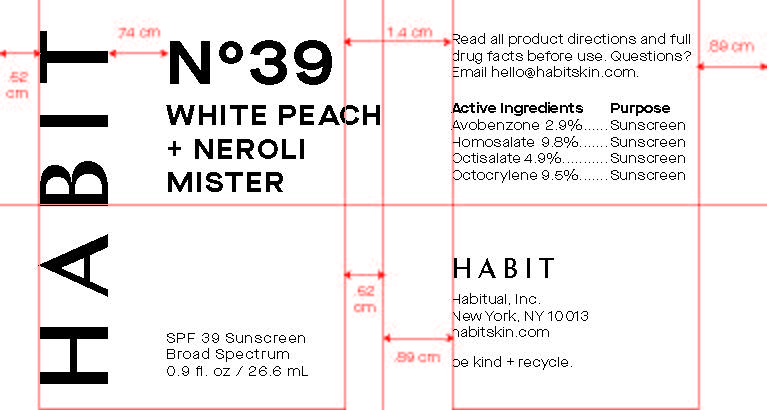 DRUG LABEL: Habit SPF 39 White Peach and Neroli Mister
NDC: 76150-366 | Form: SPRAY
Manufacturer: Bell International Laboratories, Inc
Category: otc | Type: HUMAN OTC DRUG LABEL
Date: 20220826

ACTIVE INGREDIENTS: OCTISALATE 4.9 g/100 mL; AVOBENZONE 2.9 g/100 mL; HOMOSALATE 9.8 g/100 mL; OCTOCRYLENE 9.5 g/100 mL
INACTIVE INGREDIENTS: ORANGE; LIME (CITRUS); MENTHA ARVENSIS LEAF OIL; GRAPEFRUIT; BITTER ALMOND OIL; PEACH; CITRUS AURANTIUM LEAFY TWIG; DICAPRYL SUCCINATE; POVIDONE, UNSPECIFIED; BUTYLOCTYL SALICYLATE; CAPRYLOYL GLYCERIN/SEBACIC ACID COPOLYMER (2000 MPA.S); DICAPRYLYL ETHER; LEVOMENOL; ETHYL FERULATE; ISONONYL ISONONANOATE; ALCOHOL; DIHEPTYL SUCCINATE; MEDIUM-CHAIN TRIGLYCERIDES

Habit SPF 39 White Peach and Neroli Mister

Active Ingredient

Avobenzone 2.9%

Homosalate 9.8%

Octisalate 4.9%

Octocrylene 9.5%

Purpose

Sunscreen

Uses

Helps prevent sunburn

If used as directed with other sun protection measures (see Directions), decreases the risk of skin cancer and early skin aging caused by the sun.

Warnings

For external use only

Do not use on damaged or broken skin

When using this producty keep out of eyes. Rinse wtih water to remove.

Stop use and ask a doctor if rash occurs

Flammable. Keep away from fire or spark.

Keep out of reach of children. If swallowed, get medical help or contact a Poison Control Center right away

Directions

Apply liberally and evenly 15 minutes before sun exposure

Reapply: after swimming or sweating, at least every 2 hours

Use a water-resistant sunscreen if swimming or sweating

Reapply after swimming or sweating

Sun Protection Meaures. Spending time in the sun increases your risk of skin cancer and early skin aging. To decrease this risk, regularly use a sunscreen with a broad spectrum SPF value of 15 or higher and other sun protection measures including:

-limit time in the sun, especially from 10a.m. - 2 p.m.

-wear long-sleeved shirts, pants, hats, and sunglasses.

Children under 6 monts-age: Ask a doctor

Other Information

Protect the product in this container from excessive heat and direct sun

Inactive Ingredients

Alcohol Denat., Bisabolol, Butyloctyl Salicylate, Capryloyl Glycerin/Sebacic Acid Copolymer, Citrus Aurantifolia (Lime) Fruit Extract, Citrus Aurantium Amara (Bitter Orange) Leaf/Twig Extract, Citrus Aurantium Dulcis (Orange) Fruit Extract, Citrus Paradisi (Grapefruit) Fruit Extract, Dicaprylyl Ether, Diheptyl Succinate, Diisooctyl Succinate, Ethyl Ferulate, Helianthus Annuus (Sunflower) Seed Oil, Isononyl Isononanoate, Mentha Arvensis Leaf Oil, Prunus Amygdalus Amara (Bitter Almond) Kernel Oil, Prunus Persica (Peach) Fruit Extract, PVP